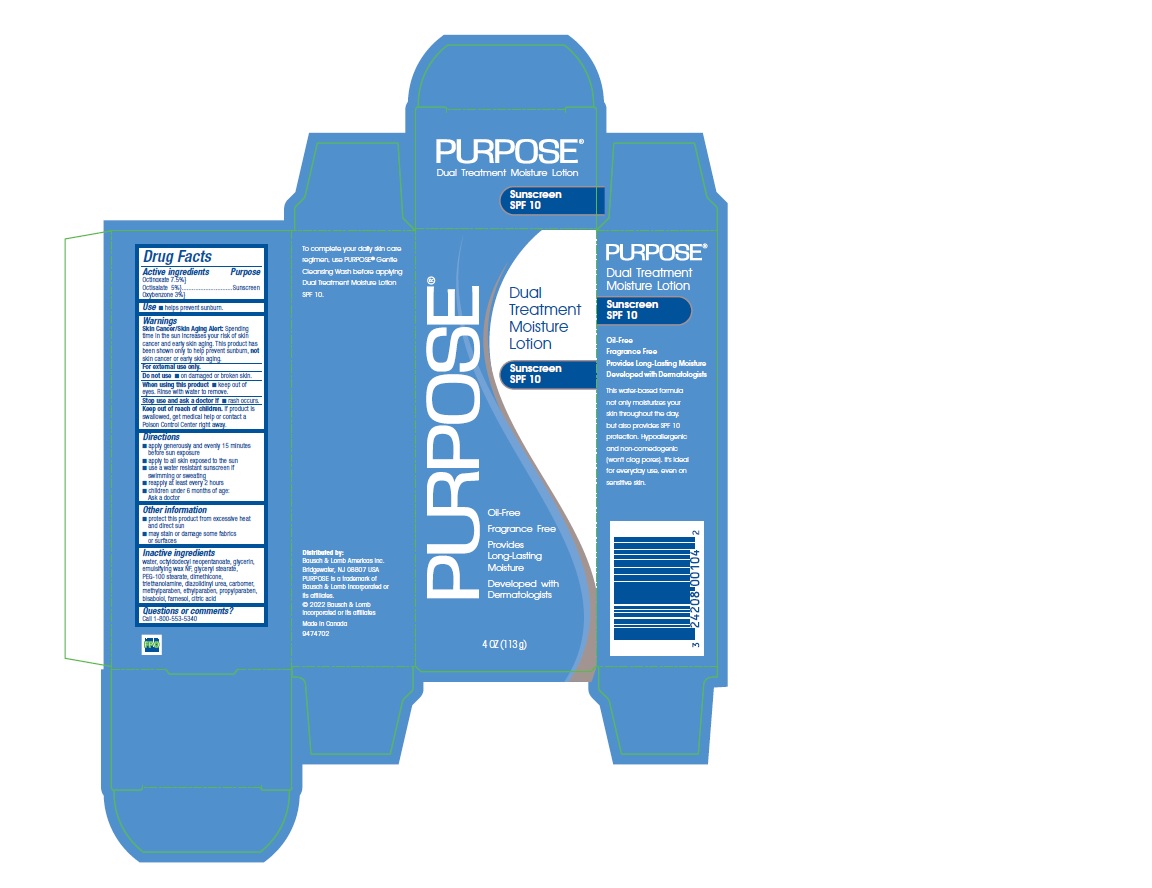 DRUG LABEL: PURPOSE
NDC: 24208-001 | Form: LOTION
Manufacturer: Bausch & Lomb Incorporated
Category: otc | Type: HUMAN OTC DRUG LABEL
Date: 20240925

ACTIVE INGREDIENTS: OCTINOXATE 7.5 g/100 g; OCTISALATE 5 g/100 g; OXYBENZONE 3 g/100 g
INACTIVE INGREDIENTS: WATER; OCTYLDODECYL NEOPENTANOATE; GLYCERIN; GLYCERYL MONOSTEARATE; PEG-100 STEARATE; DIMETHICONE; TROLAMINE; DIAZOLIDINYL UREA; METHYLPARABEN; ETHYLPARABEN; PROPYLPARABEN; LEVOMENOL

Drug Facts

Active ingredients

Octinoxate 7.5%
Octisalate 5%
Oxybenzone 3%

Purpose

Sunscreen

Use

■ helps prevent sunburn.

Warnings

Skin Cancer/Skin Aging Alert:Spending
time in the sun increases your risk of skin
cancer and early skin aging. This product has
been shown only to help prevent sunburn, not
skin cancer or early skin aging.

For external use only.

Do not use ■ on damaged or broken skin.

When using this product ■ keep out of
eyes. Rinse with water to remove.

Stop use and ask a doctor ■ if rash occurs.

Keep out of reach of children.

If product is
swallowed, get medical help or contact a
Poison Control Center right away.

Directions

■ apply generously and evenly 15 minutes
before sun exposure
■ apply to all skin exposed to the sun
■ use a water resistant sunscreen if
swimming or sweating
■ reapply at least every 2 hours
■ children under 6 months of age:
Ask a doctor

Other information

■ protect this product from excessive heat
and direct sun
■ may stain or damage some fabrics
or surfaces

Inactive ingredients

water, octyldodecyl neopentanoate, glycerin,
emulsifying wax NF, glyceryl stearate,
PEG-100 stearate, dimethicone,
triethanolamine, diazolidinyl urea, carbomer,
methylparaben, ethylparaben, propylparaben,
bisabolol, farnesol, citric acid

Questions or comments?

Call 1-800-553-5340

Principal Display Panel

PURPOSE®

Dual
Treatment
Moisture
Lotion

Sunscreen
SPF 10

Oil-Free
Fragrance Free
Provides
Long-Lasting
Moisture
Developed with
Dermatologists
4 OZ (113g)

9474702